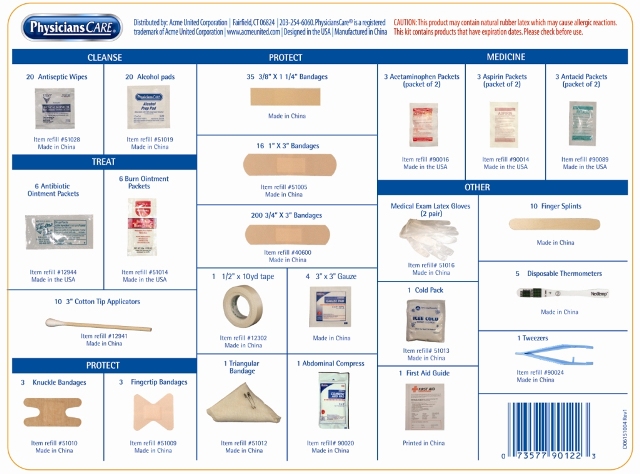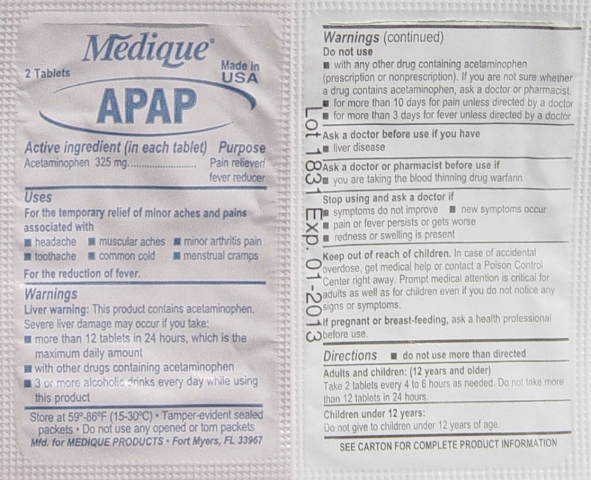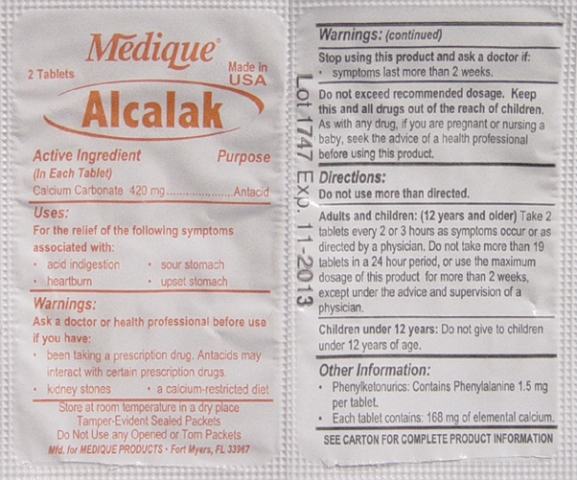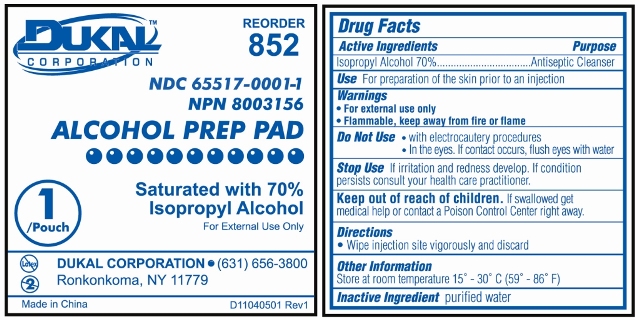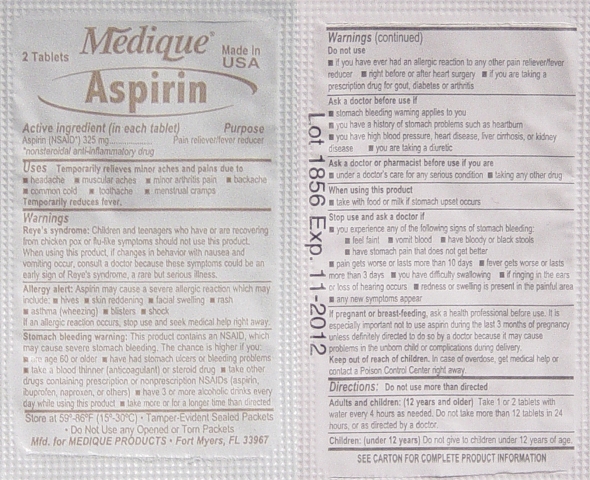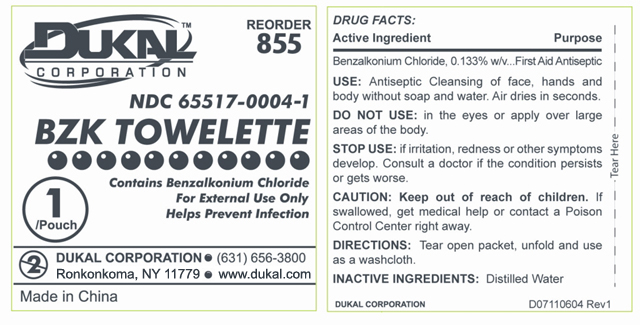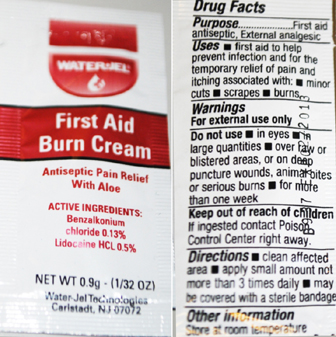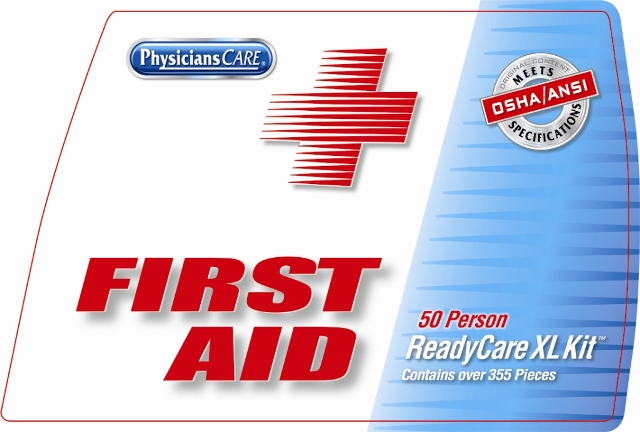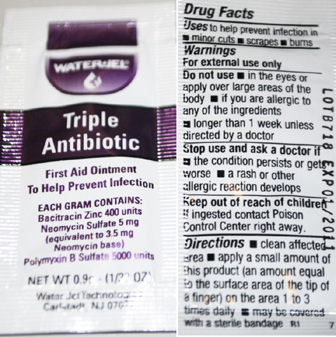 DRUG LABEL: Ready Care XL Kit
NDC: 65517-0021 | Form: KIT | Route: TOPICAL
Manufacturer: Dukal Corporation
Category: other | Type: MEDICAL DEVICE
Date: 20101103

ACTIVE INGREDIENTS: ISOPROPYL ALCOHOL 0.70 mL/1.0 mL; BACITRACIN ZINC 400 [iU]/1 g; NEOMYCIN SULFATE 3.5 mg/1 g; POLYMYXIN B SULFATE 5000 [iU]/1 g; BENZALKONIUM CHLORIDE 0.13 g/100 g; LIDOCAINE HYDROCHLORIDE 0.5 g/100 g; BENZALKONIUM CHLORIDE 0.00186 mL/1.4 mL; ACETAMINOPHEN 325 mg/1 1; ASPIRIN 325 mg/1 1; Calcium Carbonate 420 mg/1 1
INACTIVE INGREDIENTS: PETROLATUM; EDETATE DISODIUM; LIGHT MINERAL OIL; STEARIC ACID; POLYETHYLENE GLYCOL; CETYL ALCOHOL; TROLAMINE; GLYCERIN; METHYLPARABEN; PROPYLENE GLYCOL; DIAZOLIDINYL UREA; ALOE VERA LEAF; WATER; PROPYLPARABEN; GLYCERYL MONOSTEARATE; WATER 1.39814 mL/1.4 mL; HYPROMELLOSE; POLYETHYLENE GLYCOL; POVIDONE; STARCH, CORN; STEARIC ACID; HYPROMELLOSE; POLYETHYLENE GLYCOL; PROPYLENE GLYCOL; STARCH, CORN; D&C YELLOW NO. 10; MAGNESIUM STEARATE; SILICON DIOXIDE; STARCH, CORN; SUCROSE

Front Label

PACKAGE LABEL

Physicians Care

FIRST AID

50 Person

ReadyCare XL Kit

Contains over 355 Pieces

Back Label

Physicians Care

CLEANSE

20 Antiseptic Wipes
20 Alcohol Pads

TREAT

6 Antibiotic Ointment Packets
6 Burn Ointment Packets
10 3" Cotton Tip Applicators

PROTECT

3 Knuckle Bandages
3 Fingertip Bandages
35 3/8” x 1 1/2” Bandages
16 1” x 3” Bandages
200 3/4” x 3” Bandages
1 1/2" Tape
1 Triangular Bandage
4 3" x 3" Sterile Gauze Pads
1 Abdominal Compress

Medicine

3 Acetaminophen Packets (packet of 2)
3 Aspirin Packets (packets of 2)
3 Antacid Packets (packets of 2)

Other

Gloves (2 Pair)
1 Cold Pack
1 First Aid Guide
10 Finger Splints
5 Disposable Thermometers
1 Tweezer

Acme United Corporation
60 Round Hill Road
Fairfield CT 06824
www.acmeunited.com
Designed in the USA | Made in China
CAUTION: This product may contain natural rubber latex which may cause allergic reactions.
This kit contains products that have expiration dates. Please check before use.

BZK Towelette Labeling

Reorder 855

NDC 65517-0004-1

Dukal

BZK TOWELETTE

Contains Benzalkonium Chloride

For External Use Only

Helps Prevent Infection

1 / Pouch

DUKAL CORPORATION

(631) 656-3800

Ronkonkoma, NY 11779 www.dukal.com

Made in China

Drug Facts

Active Ingredients....................Benzalkonium Chloride 0.133% w/v

Purpose................................. First Aid Antiseptic

USE: Antiseptic Cleansing of face, hands and
body without soap and water. Airs dries in seconds

DO NOT USE: in the eyes or apply over large
areas of the body.

STOP USE: If irritation, redness or other symptoms
develop. Consult a doctor if the conditions persists
or gets worse.

CAUTION: Keep out of reach of children. If
swallowed get medical help or contact a Poison
Control Center right away.

DIRECTIONS: Tear open packet, unfold and use
as a washcloth.

INACTIVE INGREDIENTS: Distilled Water

Prep Pad Labeling

Reorder 852

Dukal Corporation

NDC 65517-0001-1

NPN 80003156

ALCOHOL PREP PAD

Saturated with 70% Isopropyl Alcohol

For External Use Only

1 / Pouch

Dukal Corporation

Ronkonkoma, NY 11779

631-656-3800

www.dukal.com

Made in China

Drug Facts

Active Ingredients

Isopropyl Alcohol 70%

Purpose

Antiseptic Cleanser

Use

For Preparation of Skin prior to an injection

Warnings

- For External Use Only
- Flammable, Keep away from fire or flame

Do Not Use

- with electrocautery procedures
- In the Eyes. If contact occurs, flush eyes with water

Stop Use

If irritation and redness develop. If condition persists, consult your health care practitioner.

Keep out of reach of children

If swallowed, get medical help or contact a Poison Control Center right away.

Directions

Wipe injection site vigorously and discard.

Other Information

Store at Room Temperature 15 - 30 C (59 - 86 F)

Inactive Ingredient

purified water

Triple Antibiotic Labeling

WaterJel

Triple Antibiotic

First Aid Ointment

To Help Prevent Infection

Each Gram contains

Bacitracin Zinc 400 units

Neomycin Sulphate 5 mg

(equivalent to 3.5 mg Neomycin base)

Polymyxin B Sulfate 5000 units

Water-Jel Technologies

Carlstadt, NJ 07072

Drug Facts

Uses to help prevent infection in

minor cuts, scrapes, burns

Warnings

For external use only

Do not use

in the eyes or apply over large areas of the body

If you are allergic to any of the ingredients

longer than 1 week unless directed by a doctor

Stop use and ask a doctor if

the condition persists or gets worse

a rash or other allergic reaction develops

Keep out of reach of children

if ingested contact Poison Control Center right away

Directions

clean affected area apply a small amount of product

(an amount equal to the surface area of the tip of a finger)

on the area 1 to 3 times daily may be covered with a sterile bandage

First Aid Burn Cream Labeling

WaterJel

First Aid Burn Cream

Antiseptic Pain Relief with Aloe

Active Ingredients:

Benzalkonium Chloride 0.13%

Lidocaine HCL 0.5%

Water-Jel Technologies

Carlstadt, NJ 07072

Drug Facts

Purpose

First Aid Antiseptic, External analgesic

Uses

first aid to help prevent infection and for temporary

relief of pain an itching associated with minor cuts,

scrapes, burns

Warnings

For external use only

Do not use

in the eyes

in large quantities over raw or blistered areas or on

deep puncture wounds, animal bites, or serious burns

Keep out of reach of children

if ingested contact Poison Control Center right away

Directions

clean affected area apply a small amount not more

than 3 times daily may be covered with a sterile bandage

Other Information

Store at room temperature

APAP Labeling

Drug Facts
Active Ingredients (In each tablet)...............Purposes
Acetaminophen 325 mg.............................Pain Reliever/Fever Reducer
Uses:
For the temporary relief of minor aches and pains associated with:
• headache • muscular aches • minor arthritis pain
• common cold • toothache • menstrual cramps
For the reduction of fever.
Warnings:
Alcohol Warning: If you consume 3 or more alcoholic drinks every day,
ask your doctor whether you should take acetaminophen or other pain
relievers/fever reducers. Acetaminophen may cause liver damage.
Do not use:
• with any other product containing acetaminophen
• for more than 10 days for pain unless directed by a doctor
• for more than 3 days for fever unless directed by a doctor
Stop Using and Ask a Doctor If:
• symptoms do not improve
• new symptoms occur
• pain or fever persists or gets worse
• redness or swelling is present
Do not exceed recommended dosage. Keep this and all drugs out of the reach of children.
In case of accidental overdose, contact a physician or Poison Control Center immediately.
Prompt medical attention is critical for adults as well as for children even if you do not notice
any signs or symptoms.
If pregnant or breast feeding, ask a health professional before use.
Directions:
Do not use more than directed
Adults and children: (12 years and older)
Take 2 tablets every 4 to 6 hours as needed. Do not take more than 12 tablets in 24 hours,
or as directed by a doctor.
Children under 12 years:
Do not give to children under 12 years of age.
Other Information:
• Store at room temperature
• Tamper-Evident Sealed Packets
• Do Not Use any Opened or Torn Packets
Inactive Ingredients:
Corn starch*, croscarmellose sodium, crospovidone, hypromellose, microcrystalline cellulose,
mineral oil, opadry clear, pharmaceutical glaze, polyethylene glycol, povidone*, pregelatinized
starch*, sodium carboxymethylcellulose, sodium starch glycolate, stearic acid*, talc*, titanium dioxide.
*may contain
Questions or comments? 1-800-634-7680

Alcalak Labeling

Drug Facts
Active Ingredients (In each tablet)....................Purposes
Calcium Carbonate 420 mg ..............................Antacid
Uses:
For the relief of the following symptoms associated with:
• acid indigestion • sour stomach • heartburn • upset stomach
Warnings:
Ask a doctor or health professional before use if you have:
• been taking a prescription drug. Antacids may interact with certain prescription drugs.
• kidney stones
• a calcium-restricted diet
Stop using this product and ask a doctor if:
• symptoms last more than 2 weeks
Do not exceed recommended dosage.
Keep this and all drugs out of the reach of children. If you are pregnant or breast feeding,
ask a health professional before use.
Directions:
• Do not use more than directed
Adults and children: (12 years and older)
Take 2 tablets every 2 or 3 hours as symptoms occur or as directed by a physician. Do not
take more than 19 tablets in a 24 hour period, or use the maximum dosage of this product for
more than 2 weeks, except under the advice and supervision of a physician.
Children under 12 years:
Do not give to children under 12 years of age.
Other Information:
• Phenylketonurics: Contains Phenylalanine 1.5 mg per tablet
• Each tablet contains 168 mg of elemental calcium
• Store at room temperature in a dry place
• Tamper-Evident Sealed Packets
• Do not Use any Opened or Torn Packets
Inactive Ingredients:
aspartame*, carageenan*, croscarmellose sodium*, glycine*, magnesium stearate, mint flavor*,
silica*, sorbitol, spearmint flavor*, stearic acid*, stevix*, xylitol*
*may contain
Questions or comments? 1-800-634-7680

Aspirin Labeling

Drug Facts
Active Ingredients (In each tablet)..................Purposes
Aspirin 325mg (NSAID*) ...............................Pain Reliever / Fever Reducer
*nonsteroidal anti-inflammatory drug
Uses:
Temporarily relieves minor aches and pains due:
• headache • muscular aches • minor arthritis pain • backache
• common cold • toothache • menstrual cramps
Temporarily reduces fever.
Warnings:
Reye's Syndrome: Children and teenagers should not use this medicine for chicken pox,
or flu symptoms before a doctor is consulted about Reye's Syndrome, a rare but serious
illness reported to be associated with aspirin.
Allergy Alert: Aspirin may cause a severe allergic reaction which may include:
• hives • skin reddening • facial swelling • rash • asthma (wheezing) • blisters • shock
If an allergic reaction occurs, stop use and seek medical help right away.
Stomach Bleeding Warning: This product contains a nonsteroidal anti-inflammatory
drug (NSAID), which may cause stomach bleeding.
The chance is higher if you:
• are age 60 or older • have had stomach ulcers or bleeding problems
• take a blood thinning (anticoagulant) or steroid drug
• take other drugs containing an NSAID (aspirin, ibuprofen, naproxen, or others)
• have 3 or more alcohol drinks every day while using this product
• take more or for a longer time than directed
Do not use:
• if you have ever had an allergic reaction to any other pain reliever/ fever reducer.
• right before or after heart surgery
Ask a Doctor before use if you have:
• problems or serious side effects from taking pain relievers or fever reducers
• stomach problems that last or come back, such as heartburn, upset stomach, or
stomach pain • ulcers • bleeding problems • high blood pressure
• heart or kidney disease • taken a diuretic • reached age 60 or older
Ask a Doctor or Pharmacist before use if you are:
• taking any other drug containing and NSAID (prescription or nonprescription)
• taking a blood thinning (anticoagulant) or steroid drug
• under a doctor’s care for any serious condition • taking any other drug
When using this product:
• take with food or milk if stomach upset occurs
• long term continuous use may increase the risk of heart attack or stroke
Stop Using and Ask a Doctor If:
• you feel faint, vomit blood, or have bloody or black stools. These are signs of
stomach bleeding. • pain gets worse or lasts more than 10 days
• fever gets worse or lasts more than 3 days • you have difficulty swallowing
• it feels like the pill is stuck in your throat • you develop heartburn
• stomach pain or upset gets worse or lasts
• redness or swelling is present in the painful area • any new symptoms appear
If pregnant or breast-feeding, ask a health professional before use. It is especially
important not to use aspirin during the last 3 months of pregnancy unless definitely
directed to do so by a doctor because it may cause problems in the unborn child or
complications during delivery.
Keep out of reach of children. In case of overdose, get medical help or contact a
Poison Control Center right away.
Directions:
• Do not take more than directed.
• The smallest effective dose should be used.
• Do not take longer than 10 days, unless directed by a doctor (see Warnings)
• Drink a full glass of water with each dose.
Adults and children: (12 years and older)
Take 1 or 2 tablets with water every 4 hours as needed. Do not take more than 12 tablets
in 24 hours, or as directed by a doctor.
Children under 12 years:
Do not give to children under 12 years of age.
Other Information:
• Read all product information before using
• Store at room temperature
• Avoid excessive heat and humidity
• Tamper evident sealed packets
• Do not use any opened or torn packets
Inactive Ingredients:
Corn starch, croscarmellose sodium*, hypromellose*, microcrystalline cellulose*, mineral oil*,
polyethylene glycol, propylene glycol, silicon dioxide, starch, stearic acid, talc, titanium dioxide*.
*may contain
Questions or comments? 1-800-634-7680